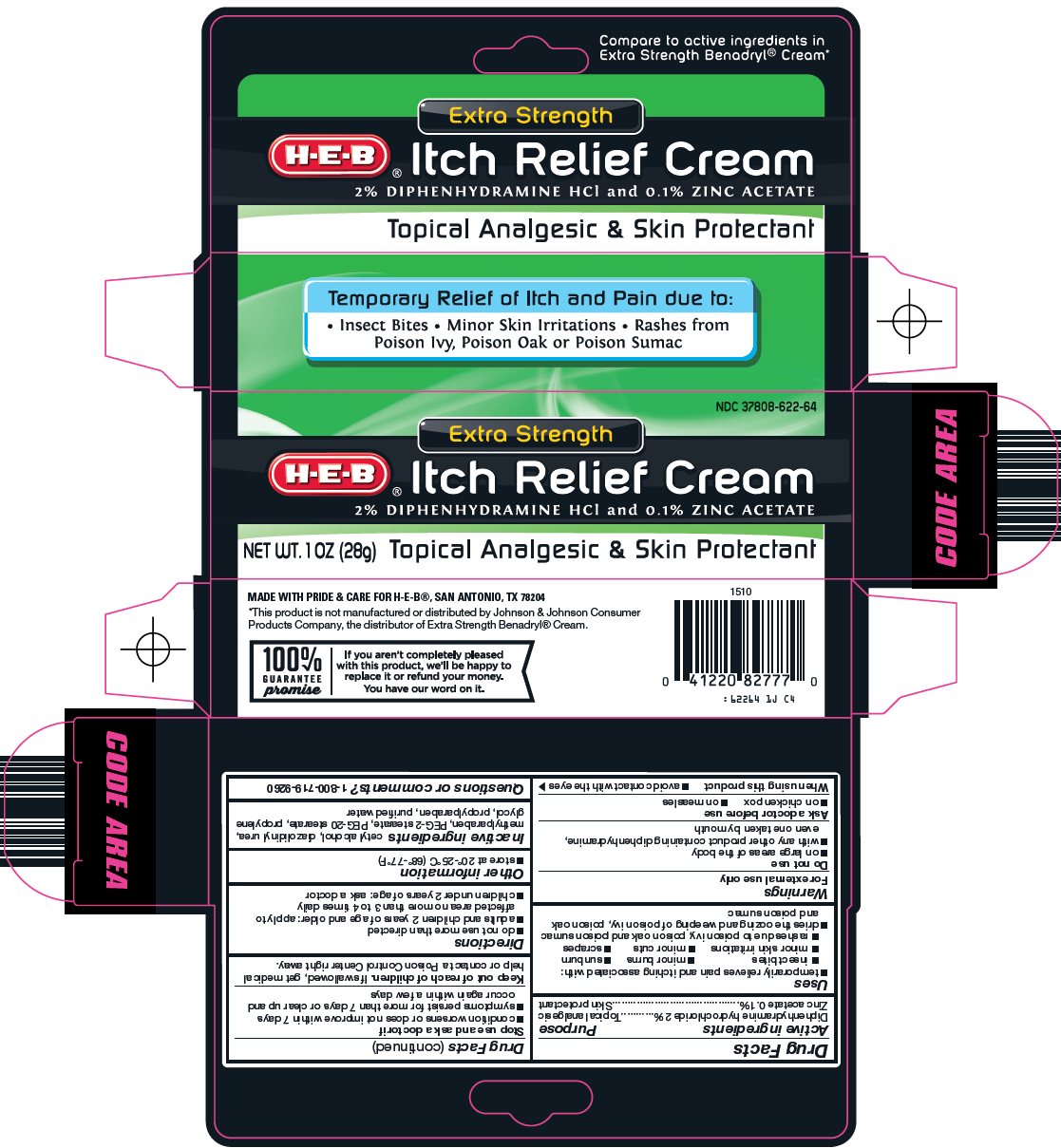 DRUG LABEL: itch relief
NDC: 37808-622 | Form: CREAM
Manufacturer: H E B
Category: otc | Type: HUMAN OTC DRUG LABEL
Date: 20241013

ACTIVE INGREDIENTS: DIPHENHYDRAMINE HYDROCHLORIDE 2 g/100 g; ZINC ACETATE 0.1 g/100 g
INACTIVE INGREDIENTS: CETYL ALCOHOL; DIAZOLIDINYL UREA; METHYLPARABEN; PROPYLENE GLYCOL; PROPYLPARABEN; WATER

HEB Itch Relief Cream Drug Facts

Active ingredient

Diphenhydramine hydrochloride 2%

Zinc acetate 0.1%

Purpose

Topical analgesic

Skin protectant

Uses

1. temporarily relieves pain and itching associated with:
2. insect bites
3. minor burns
4. sunburn
5. minor skin irritations
6. minor cuts
7. scrapes
8. rashes due to poison ivy, poison oak and poison sumac
9. dries the oozing and weeping of poison ivy, poison oak and poison sumac

Warnings

For external use only

Do not use

1. on large areas of the body
2. with any other product containing diphenhydramine, even one taken by mouth

Ask a doctor before use

1. on chicken pox
2. on measles

When using this product

1. avoid contact with the eyes

Stop use and ask a doctor if

1. condition worsens or does not improve within 7 days
2. symptoms persist for more than 7 days or clear up and occur again within a few days

Keep out of reach of children.

If swallowed, get medical help or contact a Poison Control Center right away.

Directions

1. do not use more than directed
2. adults and children 2 years of age and older: apply to affected area no more than 3 to 4 times daily
3. children under 2 years of age: ask a doctor

Other information

1. store at 20°-25°C (68°-77°F)

Inactive ingredients

cetyl alcohol, diazolidinyl urea, methylparaben, PEG-2 stearate, PEG-20 stearate, propylene glycol, propylparaben, purified water

Questions or comments?

1-800-719-9260

Principal Display Panel

Compare to active ingredients in Extra Strength Benadryl® Cream

Extra Strength

H-E-B®

Itch Relief Cream

2% DIPHENHYDRAMINE HCl and 0.1% ZINC ACETATE

Topical Analgesic & Skin Protectant

Temporary Relief of Itch and Pain due to:

• Insect Bites • Minor Skin Irritations • Rashes from Poison Ivy, Poison Oak or Poison Sumac

NET WT. 1 OZ (28g)